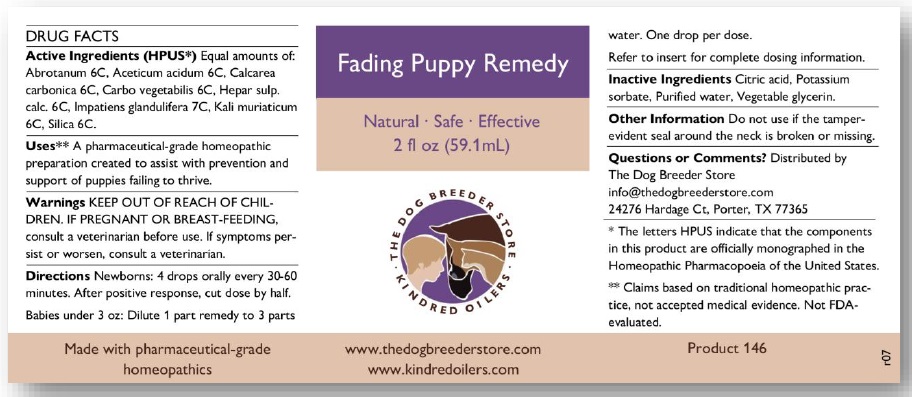 DRUG LABEL: Fading Puppy Remedy
NDC: 86214-001 | Form: LIQUID
Manufacturer: The Dog Breeder Store LLC
Category: homeopathic | Type: OTC ANIMAL DRUG LABEL
Date: 20241224

ACTIVE INGREDIENTS: ARTEMISIA ABROTANUM FLOWERING TOP 6 [hp_C]/59 mL; ACETIC ACID 6 [hp_C]/59 mL; OYSTER SHELL CALCIUM CARBONATE, CRUDE 6 [hp_C]/59 mL; ACTIVATED CHARCOAL 6 [hp_C]/59 mL; CALCIUM SULFIDE 6 [hp_C]/59 mL; IMPATIENS GLANDULIFERA FLOWER 7 [hp_C]/59 mL; POTASSIUM CHLORIDE 6 [hp_C]/59 mL; SILICON DIOXIDE 6 [hp_C]/59 mL
INACTIVE INGREDIENTS: CITRIC ACID MONOHYDRATE; POTASSIUM SORBATE; WATER; GLYCERIN

Active Ingredient

Equal amounts of: Abrotanum 6C, Aceticum acidum 6C, Calcarea carbonica 6C, Carbo vegetabilis 6C, Hepar sulp. calc. 6C, Impatiens glandulifera 7C, Kali muriaticum 6C, Silica 6C

Purpose

A pharmaceutical-grade liquid homeopathic preparation created to assist with prevention and revival for puppies failing to thrive.

Uses

A pharmaceutical-grade homeopathic preparation created to assist with prevention and support of puppies failing to thrive.

Warnings

KEEP OUT OF REACH OF CHIL DREN. IF PREGNANT OR BREAST-FEEDING, consult a veterinarian before use.

If symptoms per sist or worsen, consult a veterinarian.

Directions

Newborns: 4 drops orally every 30-60 minutes. After positive response, cut dose by half. Babies under 3 oz: Dilute 1 part remedy to 3 parts water. One drop per dose. Refer to insert for complete dosing information.

Inactive Ingredients

Citric acid, Potassium sorbate, Purified water, Vegetable glycerin.

Other information

Do not use if the tamper evident seal around the neck is broken or missing.